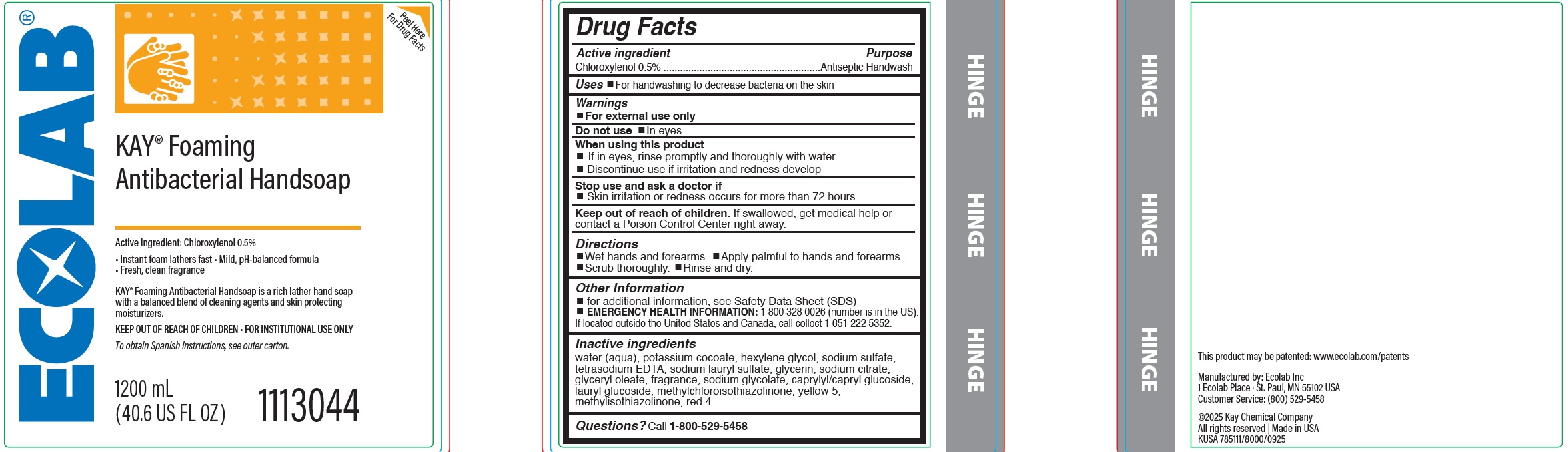 DRUG LABEL: Kay Foaming Antibacterial Handsoap
NDC: 47593-661 | Form: SOLUTION
Manufacturer: Ecolab Inc.
Category: otc | Type: HUMAN OTC DRUG LABEL
Date: 20251230

ACTIVE INGREDIENTS: CHLOROXYLENOL 5 mg/1 mL
INACTIVE INGREDIENTS: WATER; POTASSIUM COCOATE; HEXYLENE GLYCOL; SODIUM SULFATE ANHYDROUS; EDETATE SODIUM; SODIUM LAURYL SULFATE; GLYCERIN; SODIUM CITRATE; GLYCERYL OLEATE; SODIUM GLYCOLATE; CAPRYLYL/CAPRYL GLUCOSIDE; LAURYL GLUCOSIDE; METHYLCHLOROISOTHIAZOLINONE; FD&C YELLOW NO. 5; METHYLISOTHIAZOLINONE; FD&C RED NO. 4

Drug Facts

Active ingredient

Chloroxylenol, 0.5%

Purpose

Antiseptic handwash

Uses

- For handwashing to decrease bacteria on the skin.

Warnings

- For external use only

Do not use

- In eyes

When using this product

- If in eyes, rinse promptly and thoroughly with water
- Discontinue use if irritation and redness develop

Stop use and ask doctor if

Skin irritation or redness occurs for more than 72 hours

Keep out of reach of children. If swallowed, get medical help or contact a Poison Control Center right away.

Directions

- Wet hands and forearms. • Apply palmful to hands and forearms. • Scrub Thoroughly. • Rinse and dry.

Other Information

- EMERGENCY HEALTH INFORMATION: 1 800 328 0026 (number is in the US).
- If located outside the United States and Canada, call collect 1 651 222 5352

INACTIVE INGREDIENT

Inactive ingredients water (aqua), potassium cocoate, hexylene glycol, sodium sulfate, tetrasodium EDTA, sodium lauryl sulfate, glycerin, sodium citrate, glyceryl oleate, fragrance, sodium glycolate, caprylyl/capryl glucoside, lauryl glucoside, methylchloroisothiazolinone, yellow 5, methylisothiazolinone, red 4

Questions?

Questions? Call 1-800-529-5458

Representative label and Principal Display Panel

ECOLAB

Kay Foaming

Antibacterial Handsoap

Active Ingredient: Chloroxylenol 0.5%

Instant foam lathers fast • Mild, pH-balanced formula

Fresh, clean fragrance

KAY® Foaming Antibacterial Handsoap is a rich lather hand soap

with a balanced blend of cleaning agents and skin protecting

moisturizers.

KEEP OUT OF REACH OF CHILDREN • FOR INSTITUTIONAL USE ONLY

Manufactured by: Ecolab Inc

1 Ecolab Place · St. Paul, MN 55102 USA

Customer Service: (800) 529-5458

©2025 Kay Chemical Company

All rights reserved | Made in USA

KUSA 785111/8000/0925